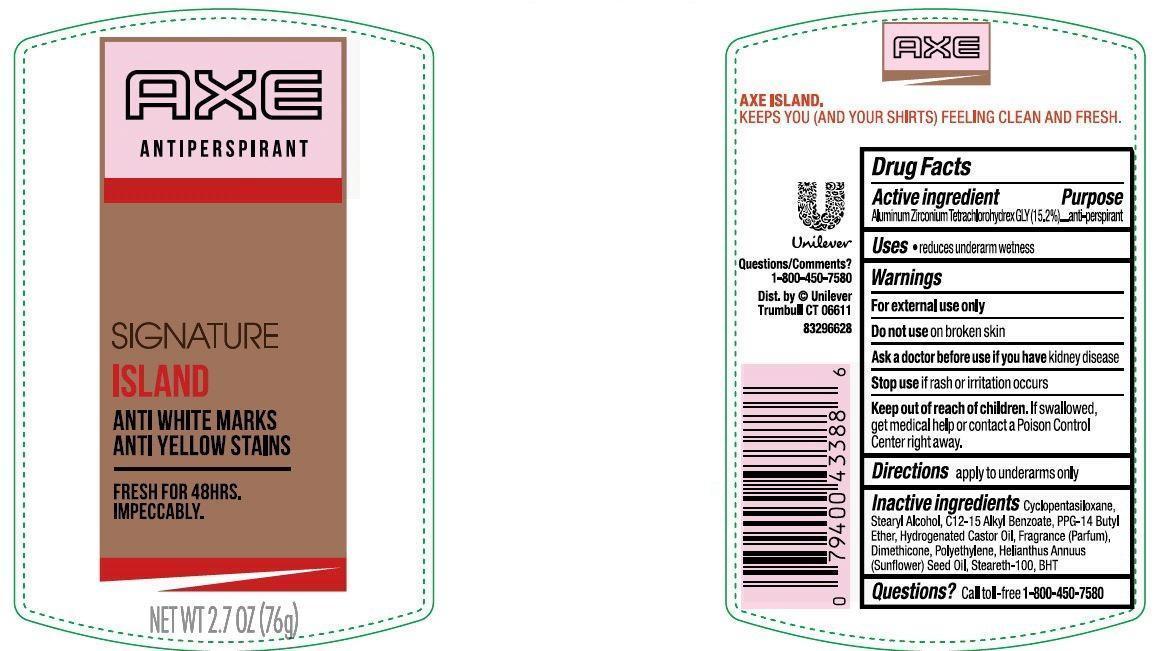 DRUG LABEL: Axe 
NDC: 64942-1420 | Form: STICK
Manufacturer: Conopco Inc. d/b/a Unilever
Category: otc | Type: HUMAN OTC DRUG LABEL
Date: 20150702

ACTIVE INGREDIENTS: Aluminum Zirconium Tetrachlorohydrex GLY 15.2 g/100 g
INACTIVE INGREDIENTS: CYCLOMETHICONE 5; PPG-14 BUTYL ETHER; STEARYL ALCOHOL; HYDROGENATED CASTOR OIL; DIMETHICONE; PEG-8 DISTEARATE; SUNFLOWER OIL; BUTYLATED HYDROXYTOLUENE

Axe Signature Island Antiperspirant Deodorant

Active ingredient

Aluminum Zirconium Tetrachlorohydrex GLY(15.2%)

Purpose

antiperspirant

Uses
· reduces underarm wetness

Warnings
For external use only

Do not use on broken skin

Ask a doctor before use if you have kidney disease

Stop use if rash or irritation occurs

Keep out of reach of children. If swallowed, get medical help or contact a Poison Control Center right away.

Directions

apply to underarms only

INACTIVE INGREDIENT

Inactive Ingredients Cyclopentasiloxane, Stearyl Alcohol, C12-15 Alkyl Benzoate, PPG-14 Butyl Ether, Hydrogenated Castor Oil, Fragrance (Parfum), Dimethicone, Polyethylene, Helianthus Annuus (Sunflower) Seed Oil, Steareth-100, BHT.

Questions?

Call toll-free 1-800-450-7580